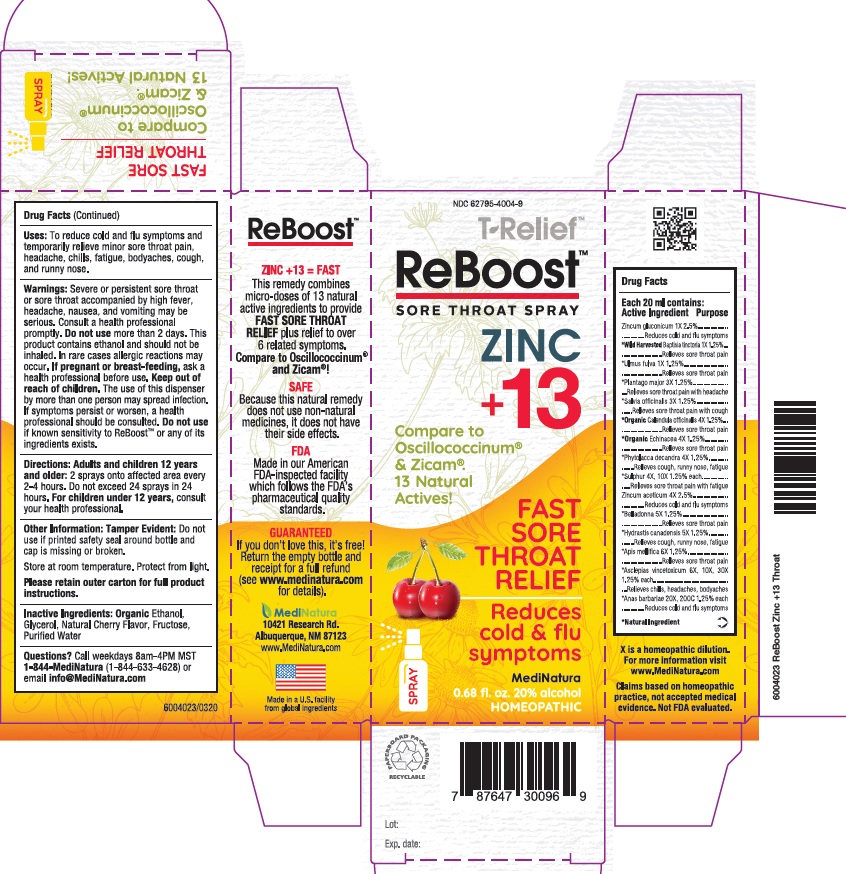 DRUG LABEL: ReBoost
NDC: 62795-4004 | Form: SPRAY
Manufacturer: MediNatura
Category: homeopathic | Type: HUMAN OTC DRUG LABEL
Date: 20220808

ACTIVE INGREDIENTS: APIS MELLIFERA 6 [hp_X]/20 mL; ATROPA BELLADONNA 5 [hp_X]/20 mL; CALENDULA OFFICINALIS FLOWERING TOP 4 [hp_X]/20 mL; ECHINACEA PURPUREA 4 [hp_X]/20 mL; GOLDENSEAL 5 [hp_X]/20 mL; PHYTOLACCA AMERICANA ROOT 4 [hp_X]/20 mL; PLANTAGO MAJOR 3 [hp_X]/20 mL; SAGE 3 [hp_X]/20 mL; ZINC GLUCONATE 1 [hp_X]/20 mL; BAPTISIA TINCTORIA ROOT 1 [hp_X]/20 mL; ULMUS RUBRA BARK 1 [hp_X]/20 mL; SULFUR 4 [hp_X]/20 mL; ZINC ACETATE ANHYDROUS 4 [hp_X]/20 mL; VINCETOXICUM HIRUNDINARIA ROOT 6 [hp_X]/20 mL; CAIRINA MOSCHATA HEART/LIVER AUTOLYSATE 20 [hp_X]/20 mL
INACTIVE INGREDIENTS: ALCOHOL; GLYCERIN; FRUCTOSE; WATER; CHERRY

ReBoost

ACTIVE INGREDIENTS

Each 20ml contains

Active Ingredients Purpose

*Apis mellifica 6X 1.25%

*Asclepias Vincetoxicum 6X 10X 30X 1.25%

*Belladonna 5X 1.25%

*Organic Calendula officinalis 4X 1.25%

*Organic Echinacea purpurea 4X 1.25%

*Hydrastis canadensis 5X 1.25%

*Phytolacca decandra 4X 1.25%

*Plantago major 3X 1.25%

*Salvia officinalis 3X 1.25%

*Zincum Gluconlcum 1X 2.5%

*Wild Harvested Baptisia Tinctoria 1X 1.25%

*Ulmus Fulva 1X 1.25%

*Sulphur 4X 10X 1.25%

*Zincum Aceticum 4X 2.5%

*Anas Barbariae 20X 200C 1.25%

*Natural Ingredients

INACTIVE INGREDIENTS

Ethanol, Glycerol, Natural Cherry Flavor, Fructose, Purified Water.

USES

To reduce cold and flu symptoms and temporary relief minor sore throat pain, headache, chills, fatigue,bodyaches, cough and runny nose.

DIRECTIONS

Directions: Adults and children 12 years and older: 2 sprays onto affected area every 2-4 hours. Do not exceed 24 sprays in 24 hours.

For Children under 12 years: consult your health professional.

WARNINGS

Severe or persistent sore throat or sore throat accompanied by high fever, headache, nausea, and vomiting may be serious. Consult a health professional promptly. Do not use more than 2 days. This product contains ethanol and should not be inhaled. In rare cases allergic reactions may occur. If pregnant or breast-feeding, ask a health professional before use. Keep out of reach of children. The use of this a by more than one person may spread infection. If symptoms persist or worsen, a health professional should be consulted. Do not use if known sensitivity to ReBoost™ or any of its ingredients exists.

KEEP OUT OF REACH OF CHILDREN

INDICATIONS

Reduces cold and flu symptoms

Releive sore throat pain, chills, head aches, body aches, cough, runny nose and fatigue